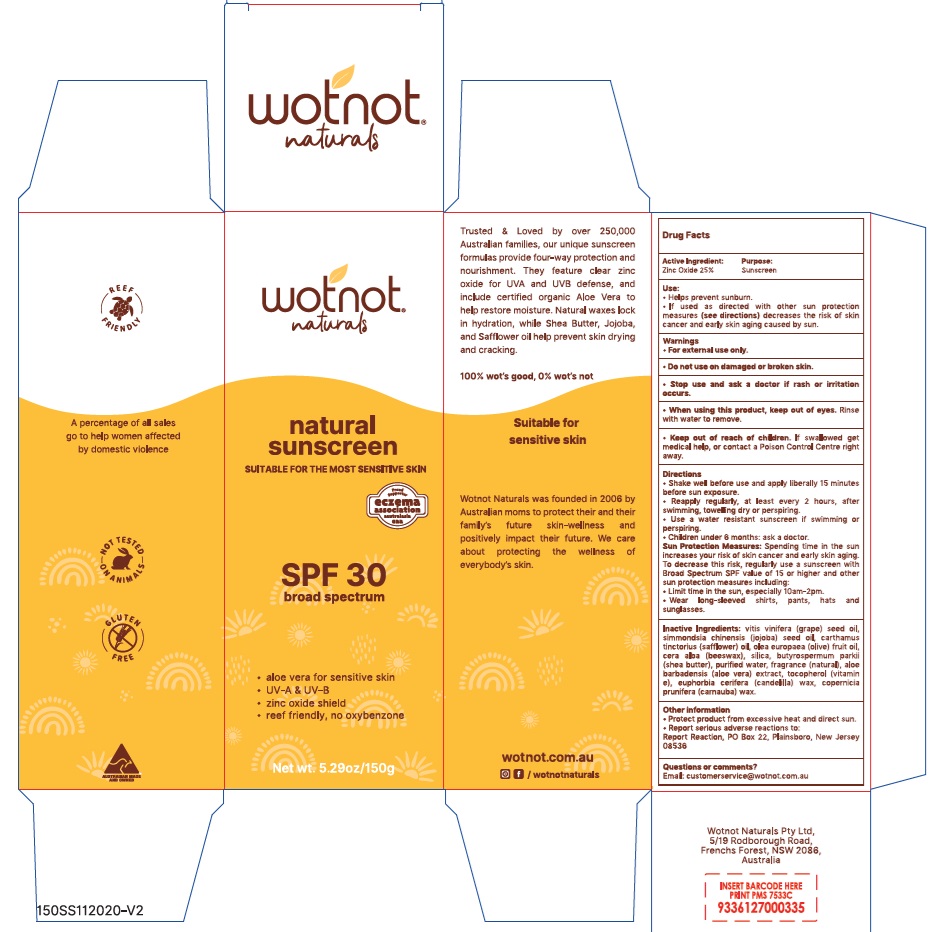 DRUG LABEL: Wotnot Naturals Natural Sunscreen SPF 30
NDC: 81486-002 | Form: LOTION
Manufacturer: ECOdirect Pty Ltd (Trading as Wotnot Naturals)
Category: otc | Type: HUMAN OTC DRUG LABEL
Date: 20241106

ACTIVE INGREDIENTS: ZINC OXIDE 250 mg/1 g
INACTIVE INGREDIENTS: TOCOPHEROL; JOJOBA OIL; CARNAUBA WAX; CANDELILLA WAX; GRAPE SEED OIL; SILICON DIOXIDE; WATER; OLIVE OIL; YELLOW WAX; SHEA BUTTER; ALOE VERA LEAF; SAFFLOWER OIL

Wotnot Naturals Natural Sunscreen SPF 30

Active Ingredient

Zinc Oxide 25%

Purpose

Sunscreen

Use

- Helps prevent sunburn.
- If used as directed with other sun protection measures (see Directions) decreases the risk of skin cancer and early skin aging caused by sun.

Warnings

For external use only.

Do not use

on damaged or broken skin.

Stop use and ask a doctor

if rash or irritation occurs.

When using this product

keep out of eyes. Rinse with water to remove.

Keep out of reach of children.

If swallowed get medical help, or contact a Poison Control Centre right away.

Directions

- Shake well before use and apply liberally 15 minutes before sun exposure.
- Reapply regularly, at least every 2 hours, after swimming, towelling dry or perspiring.
- Use a water resistant sunscreen if swimming or perspiring.
- Children under 6 months: ask a doctor.

Sun Protection Measures: Spending time in the sun increases your risk of skin cancer and early skin aging. To decrease this risk, regularly use a sunscreen with Broad Spectrum SPF value of 15 or higher and other sun protection measures including:

- Limit time in the sun, especially 10am-2pm.
- Wear long-sleeved shirts, pants, hats and sunglasses.

Inactive Ingredients

vitis vinifera (grape) seed oil, simmondsia chinensis (jojoba) seed oil, carthamus tinctorius (safflower) oil, olea europaea (olive) fruit oil, cera alba (beeswax), silica, butyrospermum parkii (shea butter), purified water, fragrance (natural), aloe barbadensis (aloe vera) extract, tocopherol (vitamin e), euphorbia cerifera (candelilla) wax, copernicia prunifera (carnauba) wax.

Other Information

- Protect product from excessive heat and direct sun.
- Report serious adverse reactions to: Report Reaction, PO Box 22, Plainsboro, New Jersey 08536

Questions or Comments?

Email: customerservice@wotnot.com.au

Company Information

Wotnot Naturals Pty Ltd, 5/19 Rodborough Road, Frenchs Forest, NSW 2086, Australia